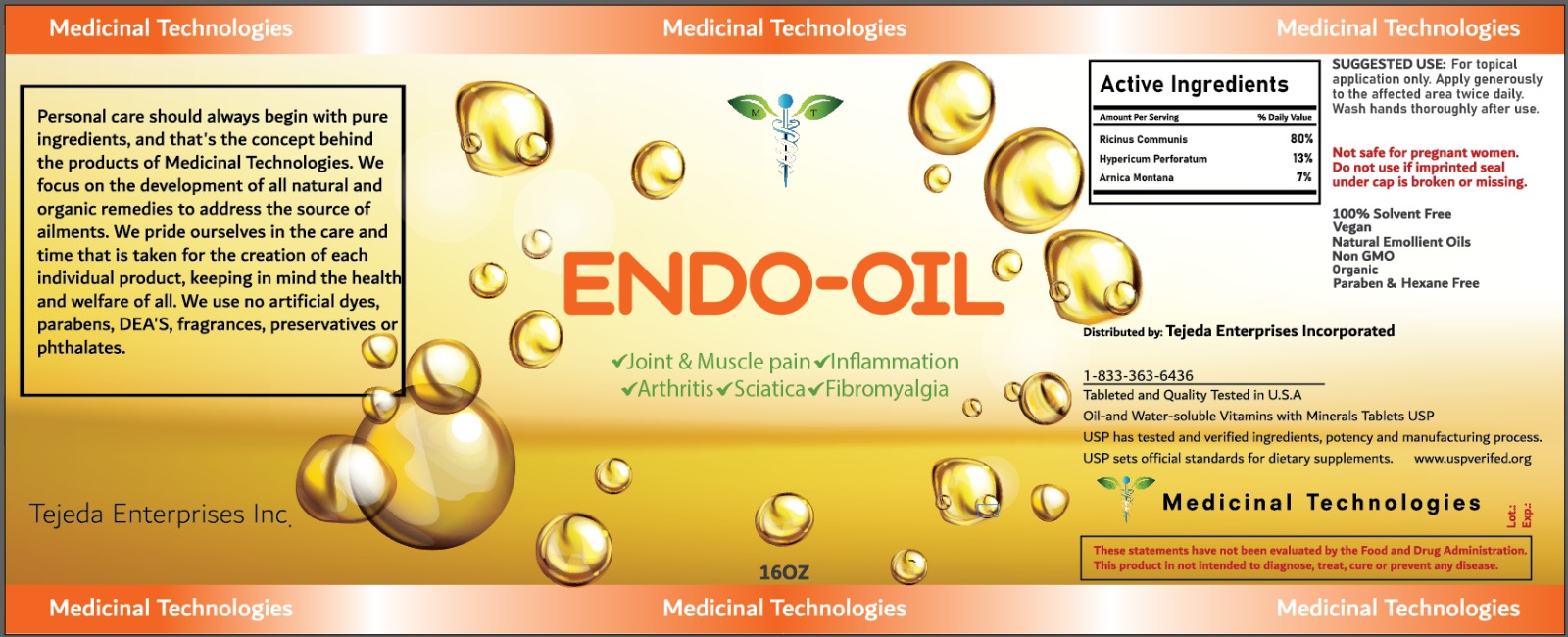 DRUG LABEL: EndoOil
NDC: 84761-0001 | Form: OIL
Manufacturer: Tejeda Enterprises Incorporated
Category: otc | Type: HUMAN OTC DRUG LABEL
Date: 20240920

ACTIVE INGREDIENTS: HYPERICUM PERFORATUM 3 g/28 g; ARNICA MONTANA 1.96 g/28 g; RICINUS COMMUNIS FIBER 22 g/28 g
INACTIVE INGREDIENTS: ARGAN OIL

DOSAGE AND ADMINISTRATION

SUGGESTED USE: For topical application only. Apply generously to the affected area twice daily. Wash hands thoroughly after use.

WARNINGS

USP has tested and verified ingredients, potency and manufacturing process. USP sets official standards for dietary supplements.

INACTIVE INGREDIENT

ARNICA MONTANA

100% Solvent Free Vegan
Natural Emollient Oils Non GMO
Organic
Paraben & Hexane Free

INDICATIONS AND USAGE

USP has tested and verified ingredients, potency and manufacturing process. USP sets official standards for dietary supplements.
Oil-and Water-soluble Vitamins with Minerals Tablets USP

keep out of reach of children section

PURPOSE

Medicinal Technologies
Personal care should always begin with pure ingredients, and that's the concept behind the products of Medicinal Technologies. We focus on the development of all natural and organic remedies to address the source of ailments. We pride ourselves in the care and time that is taken for the creation of each individual product, keeping in mind the health and welfare of all. We use no artificial dyes, parabens, DEA'S, fragrances, preservatives or phthalates.

ACTIVE INGREDIENT

HYPERICUM PERFORATUM

RICINUS COMMUNIS FIBER

PACKAGE LABEL

Medicinal Technologies
Personal care should always begin with pure ingredients, and that's the concept behind the products of Medicinal Technologies. We focus on the development of all natural and organic remedies to address the source of ailments. We pride ourselves in the care and time that is taken for the creation of each individual product, keeping in mind the health and welfare of all. We use no artificial dyes, parabens, DEA'S, fragrances, preservatives or phthalates.
Tejeda Enterprises Inc.
Medicinal Technologies
Medicinal Technologies
ENDO-OIL
Organic